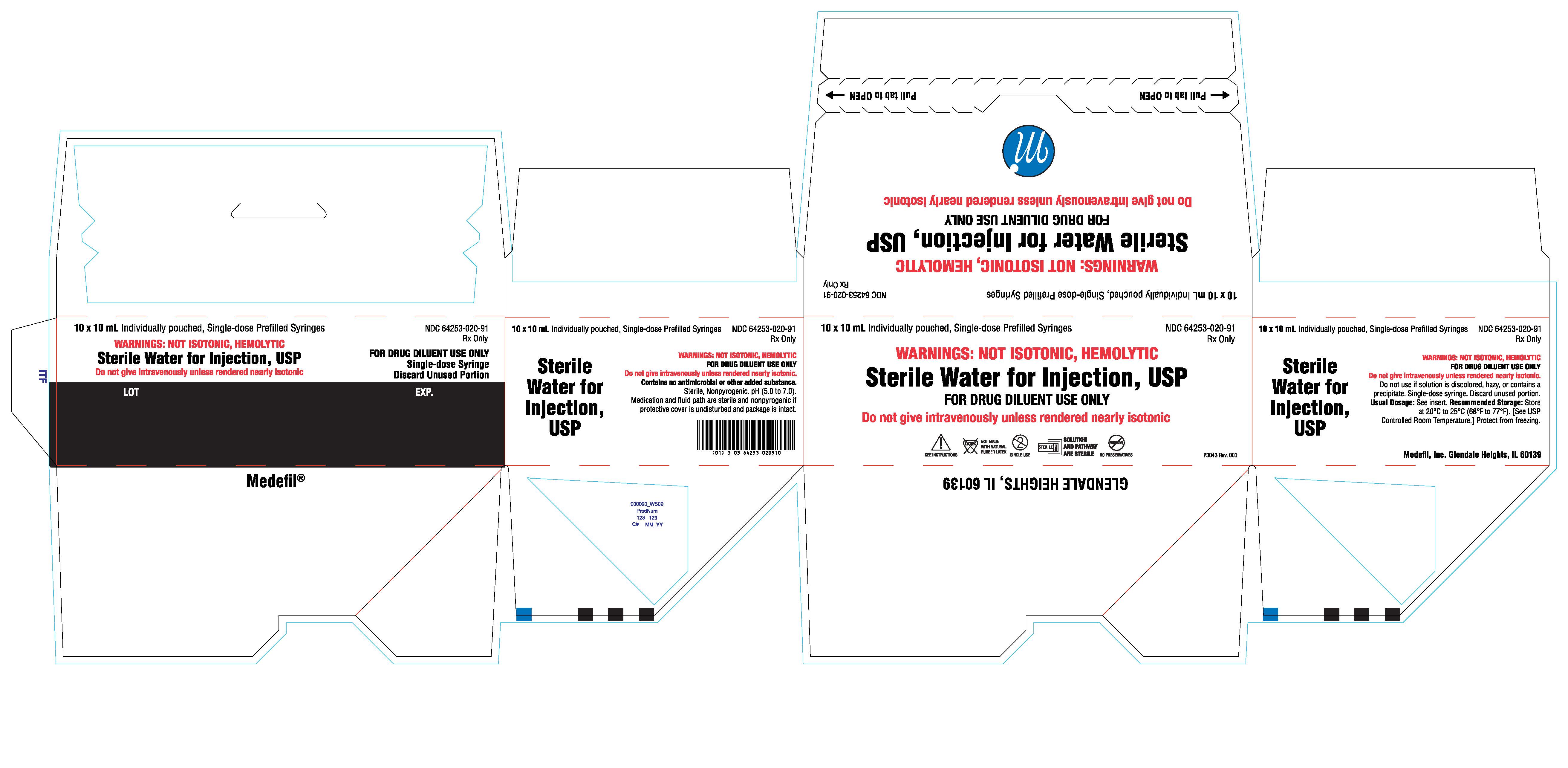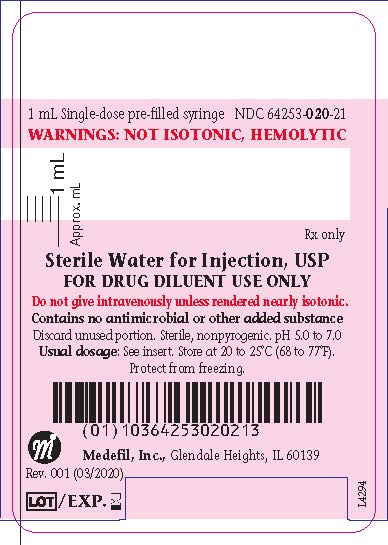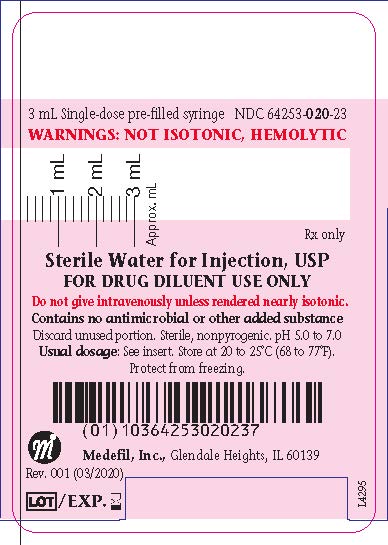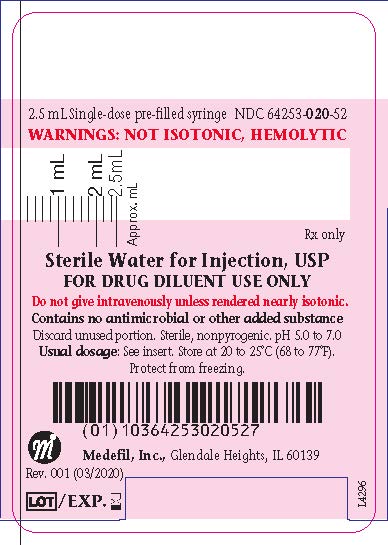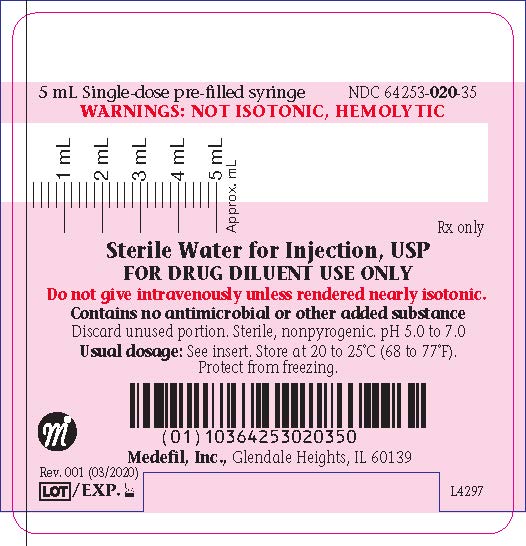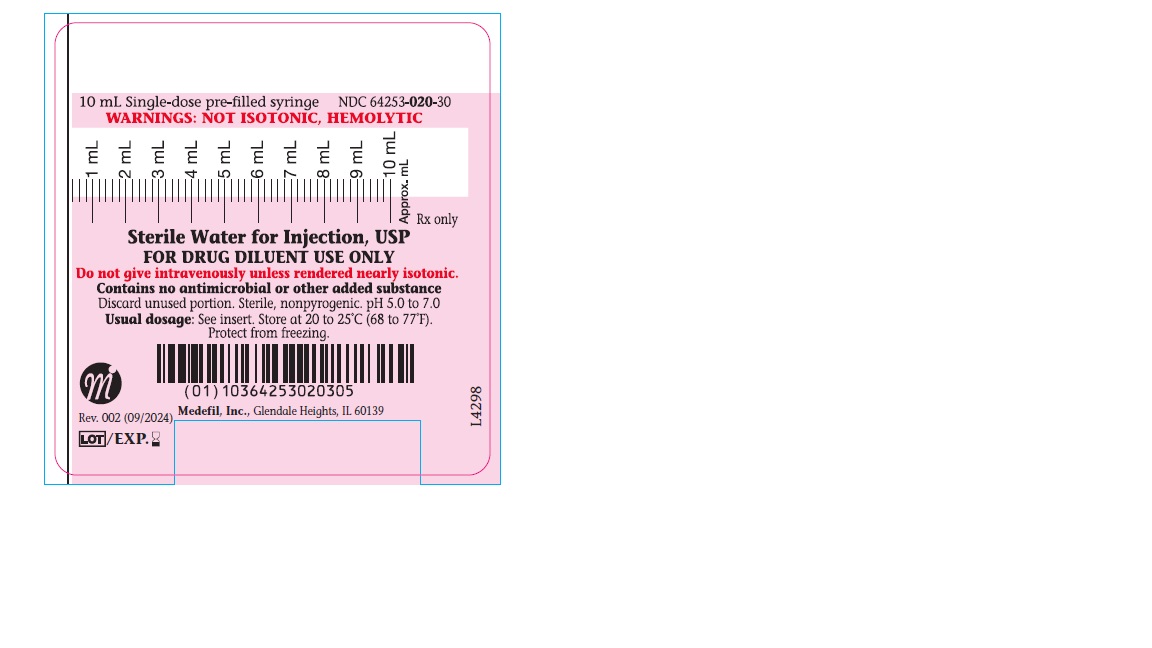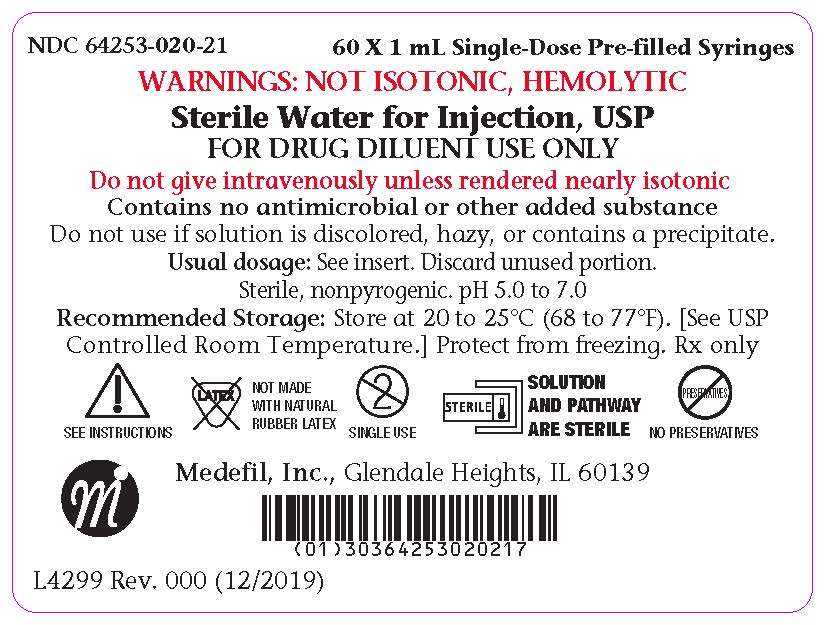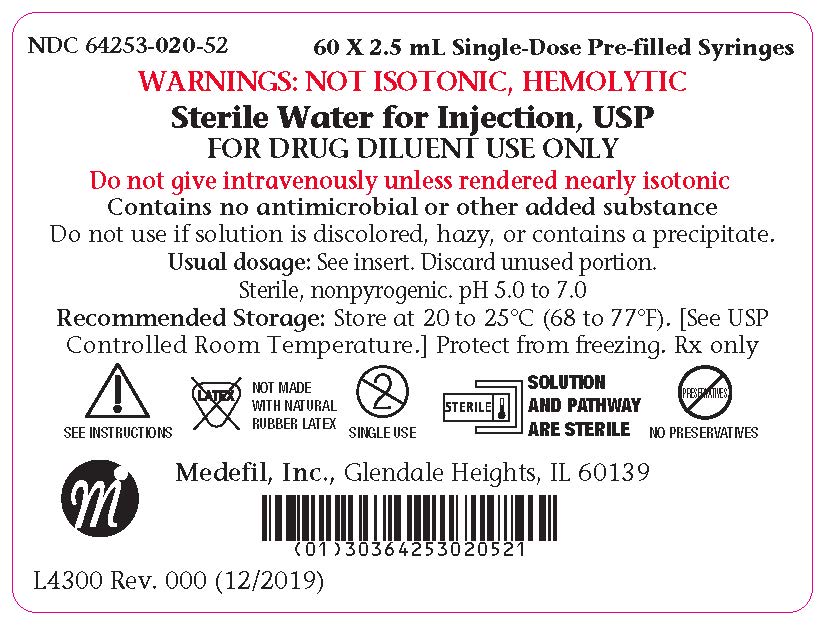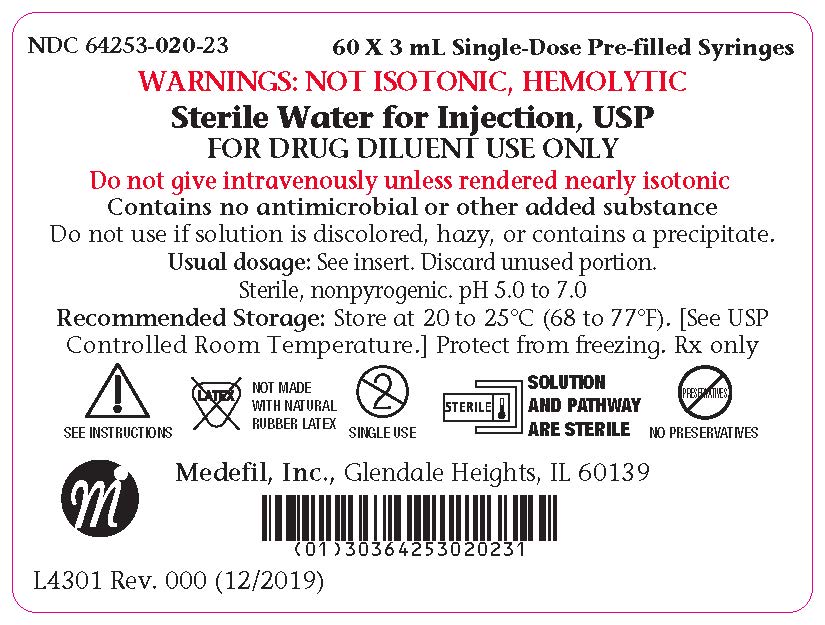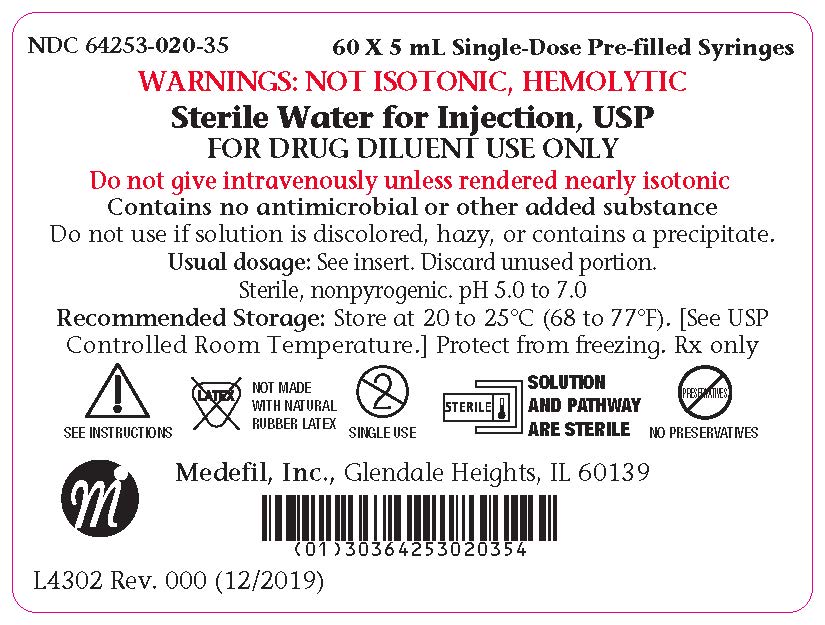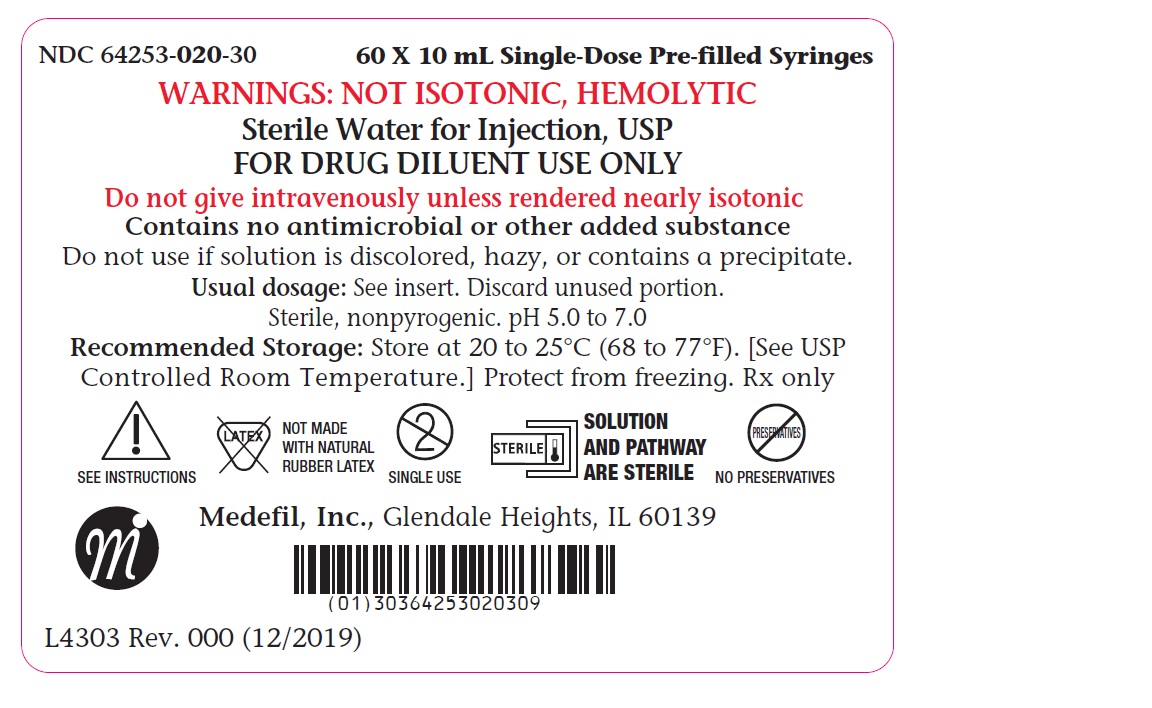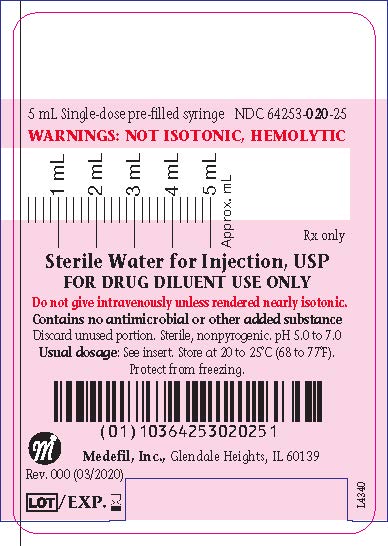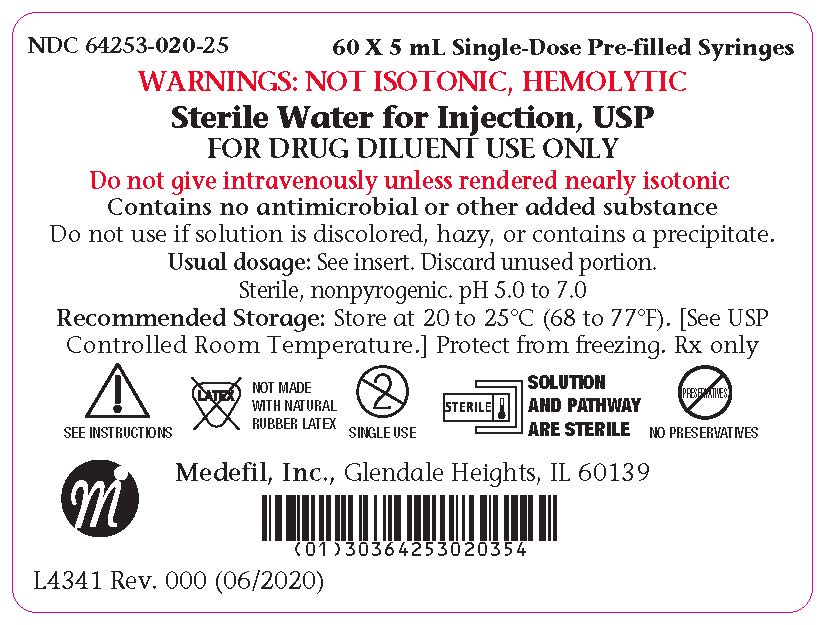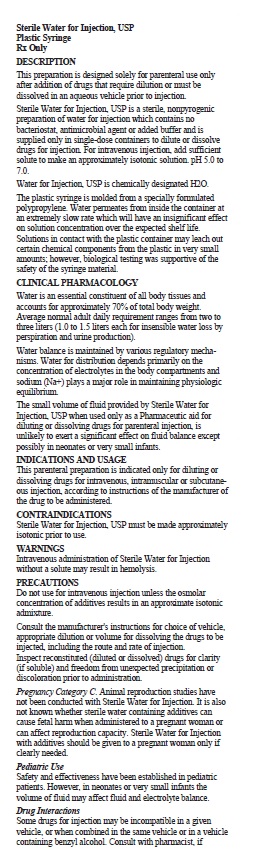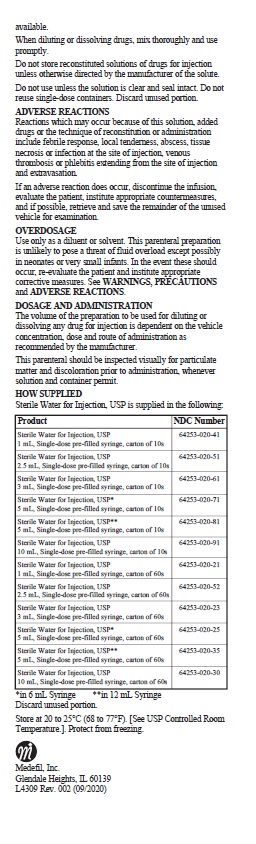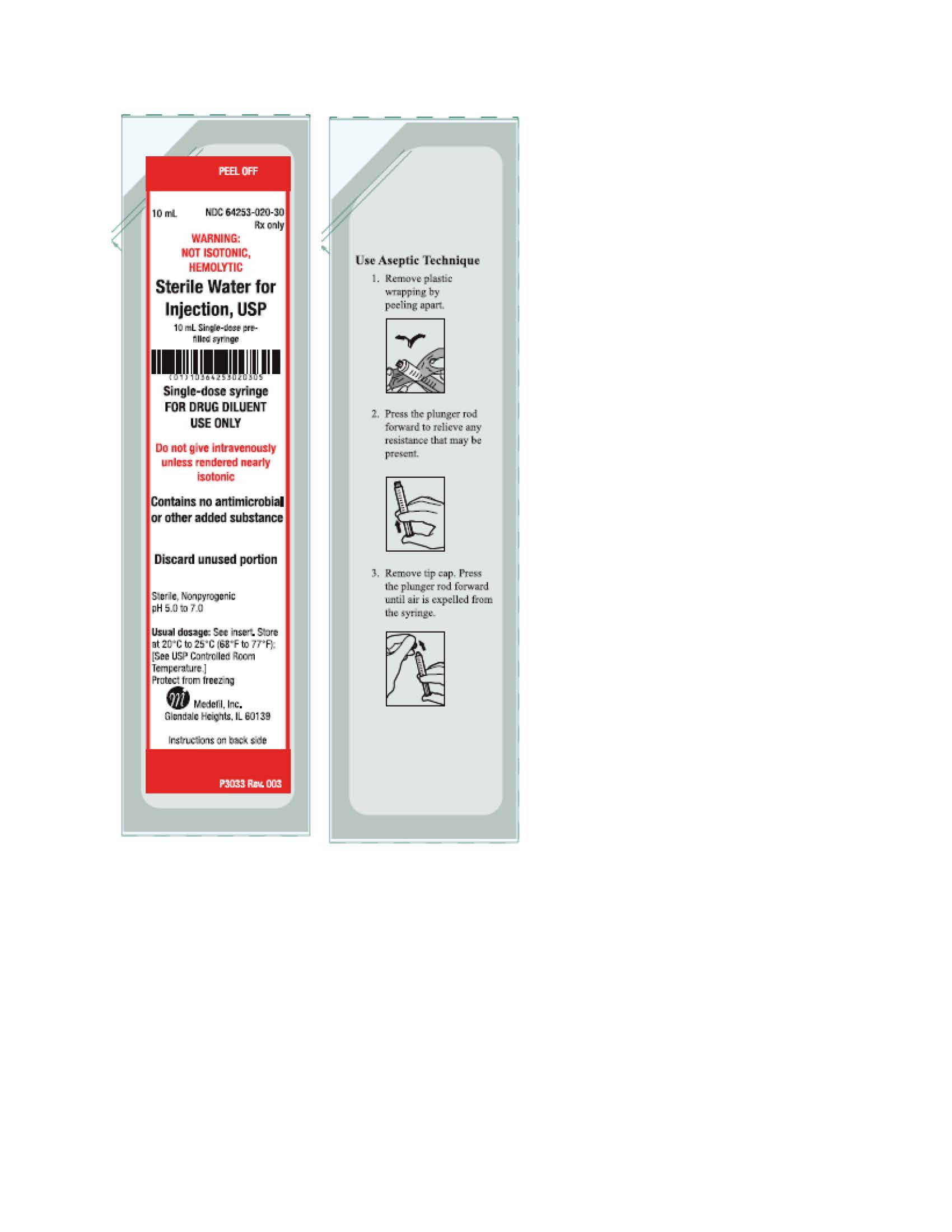 DRUG LABEL: Sterile Water
NDC: 64253-020 | Form: INJECTION, SOLUTION
Manufacturer: Medefil, Inc.
Category: prescription | Type: HUMAN PRESCRIPTION DRUG LABEL
Date: 20250108

ACTIVE INGREDIENTS: WATER 100 mL/100 mL

HIGHLIGHTS OF PRESCRIBING INFORMATION

These highlights do not include all the information needed to use STERILE WATER FOR INJECTION, USP safely and effectively. See full prescribing information for STERILE WATER FOR INJECTION, USP.
STERILE WATER FOR INJECTION, USP for Intravenous, Intramuscular, and Subcutaneous Injection
Initial U.S. Approval: 2019

INDICATIONS AND USAGE

This parenteral preparation is indicated only for diluting or dissolving drugs for intravenous, intramuscular or subcutaneous injection, according to instructions of the manufacturer of the drug to be administered.

CONTRAINDICATIONS

Sterile Water for Injection, USP must be made approximately isotonic prior to use.

DRUG INTERACTIONS

Some drugs for injection may be incompatible in a given vehicle, or when combined in the same vehicle or in a vehicle containing benzyl alcohol. Consult with pharmacist, if available.

When diluting or dissolving drugs, mix thoroughly and use promptly.

Do not store reconstituted solutions of drugs for injection unless otherwise directed by the manufacturer of the solute.

Do not use unless the solution is clear and seal intact. Do not reuse single-dose containers. Discard unused portion.

ADVERSE REACTIONS

Reactions which may occur because of this solution, added drugs or the technique of reconstitution or administration include febrile response, local tenderness, abscess, tissue necrosis or infection at the site of injection, venous thrombosis or phlebitis extending from the site of injection and extravasation.

If an adverse reaction does occur, discontinue the infusion, evaluate the patient, institute appropriate countermeasures, and if possible, retrieve and save the remainder of the unused vehicle for examination.

To report SUSPECTED ADVERSE REACTIONS, contact Medefil, Inc., at 1-630-682-4600 or www.medefilinc.com or FDA at 1-800-FDA-1088 or www.fda.gov/medwatch.

DOSAGE AND ADMINISTRATION

The volume of the preparation to be used for diluting or dissolving any drug for injection is dependent on the vehicle concentration, dose and route of administration as recommended by the manufacturer.

This parenteral should be inspected visually for particulate matter and discoloration prior to administration, whenever solution and container permit.

FULL PRESCRIBING INFORMATION

DESCRIPTION

This preparation is designed solely for parenteral use only after addition of drugs that require dilution or must be dissolved in an aqueous vehicle prior to injection.

Sterile Water for Injection, USP is a sterile, nonpyrogenic preparation of water for injection which contains no bacteriostat, antimicrobial agent or added buffer and is supplied only in single-dose containers to dilute or dissolve drugs for injection. For intravenous injection, add sufficient solute to make an approximately isotonic solution. pH 5.0 to 7.0.

Water for Injection, USP is chemically designated H2O.

The plastic syringe is molded from a specially formulated polypropylene. Water permeates from inside the container at an extremely slow rate which will have an insignificant effect on solution concentration over the expected shelf life. Solutions in contact with the plastic container may leach our certain chemical components from the plastic in very small amounts; however, biological testing was supportive of the safety of the syringe material.

CLINICAL PHARMACOLOGY

Water is an essential constituent of all body tissues and accounts for approximately 70% of total body weight. Average normal adult daily requirement ranges from two to three liters (1.0 to 1.5 liters each for insensible water loss by perspiration and urine production).

Water balance is maintained by various regulatory mechanisms. Water for distribution depends primarily on the concentration of electrolytes in the body compartments and sodium (Na+) plays a major role in maintaining physiologic equilibrium.

The small volume of fluid provided by Sterile Water for Injection, USP when used only as a Pharmaceutic aid for diluting or dissolving drugs for parenteral injection, is unlikely to exert a significant effect on fluid balance except possibly in neonates or very small infants.

INDICATIONS AND USAGE

This parenteral preparation is indicated only for diluting or dissolving drugs for intravenous, intramuscular or subcutaneous injection, according to instructions of the manufacturer of the drug to be administered.

CONTRAINDICATIONS

Sterile Water for Injection, USP must be made approximately isotonic prior to use.

WARNINGS

Intravenous administration of Sterile Water for Injection without a solute may result in hemolysis

Do not use for intravenous injection unless the osmolar concentration of additives results in an approximate isotonic admixture.

Consult the manufacturer's instructions for choice of vehicle, appropriate dilution or volume for dissolving the drugs to be injected, including the route and rate of injection.

Inspect reconstituted (diluted or dissolved) drugs for clarity (if soluble) and freedom from unexpected precipitation or discoloration prior to administration.

PREGNANCY

Pregnancy Category C. Animal reproduction studies have not been conducted with Sterile Water for Injection. It is also not known whether sterile water containing additives can cause fetal harm when administered to a pregnant woman or can affect reproduction capacity. Sterile Water for Injection with additives should be given to a pregnant woman only if clearly needed.

PEDIATRIC USE

Safety and effectiveness have been established in pediatric patients. However, in neonates or very small infants the volume of fluid may affect fluid and electrolyte balance.

DRUG INTERACTIONS

Some drugs for injection may be incompatible in a given vehicle, or when combined in the same vehicle or in a vehicle containing benzyl alcohol. Consult with pharmacist, if available.

When diluting or dissolving drugs, mix thoroughly and use promptly.

Do not store reconstituted solutions of drugs for injection unless otherwise directed by the manufacturer of the solute.

Do not use unless the solution is clear and seal intact. Do not reuse single-dose containers. Discard unused portion.

ADVERSE REACTIONS

Reactions which may occur because of this solution, added drugs or the technique of reconstitution or administration include febrile response, local tenderness, abscess, tissue necrosis or infection at the site of injection, venous thrombosis or phlebitis extending from the site of injection and extravasation.

If an adverse reaction does occur, discontinue the infusion, evaluate the patient, institute appropriate countermeasures, and if possible, retrieve and save the remainder of the unused vehicle for examination.

To report SUSPECTED ADVERSE REACTIONS, contact Medefil, Inc., at 1-630-682-4600 or www.medefilinc.com or FDA at 1-800-FDA-1088 or www.fda.gov/medwatch.

OVERDOSAGE

Use only as a diluent or solvent. This parenteral preparation is unlikely to pose a threat of fluid overload except possibly in neonates or very small infants. In the event these should occur, re-evaluate the patient and institute appropriate corrective measures. See WARNINGS, PRECAUTIONS and ADVERSE REACTIONS.

DOSAGE AND ADMINISTRATION

The volume of the preparation to be used for diluting or dissolving any drug for injection is dependent on the vehicle concentration, dose and route of administration as recommended by the manufacturer.

This parenteral should be inspected visually for particulate matter and discoloration prior to administration, whenever solution and container permit.

HOW SUPPLIED

Sterile Water for Injection, USP is supplied in the following:

Product | NDC Number
Sterile Water for Injection, USP; 1 mL, Single-dose pre-filled syriinge, carton of 10s | 64523-020-41
Sterile Water for Injection, USP; 2.5 mL, Single-dose pre-filled syringe, carton of 10s | 64253-020-51
Sterile Water for Injection, USP; 3 mL, Single-dose pre-filled syringe, carton of 10s | 64253-020-61
Sterile Water for Injection, USP*; 5 mL, Single-dose pre-filled syringe, carton of 10s | 64253-020-71
Sterile Water for Injection, USP**; 5 mL, Single-dose pre-filled syringe, carton of 10s | 64253-020-81
Sterile Water for Injection, USP; 10 mL, Single-dose pre-filled syringe, carton of 10s | 64253-020-91
Sterile Water for Injection, USP; 1 mL, Single-dose pre-filled syringe, carton of 60s | 64253-020-21
Sterile Water for Injection, USP; 2.5 mL, Single-dose pre-filled syringe, carton of 60s | 64253-020-52
Sterile Water for Injection, USP; 3 mL, Single-dose pre-filled syringe, carton of 60s | 64253-020-23
Sterile Water for Injection, USP*; 5 mL, Single-dose pre-filled syringe, carton of 60s | 64253-020-25
Sterile Water for Injection, USP**; 5 mL, Single-dose pre-filled syringe, carton of 60s | 64253-020-35
Sterile Water for Injection, USP; 10 mL, Single-dose pre-filled syringe, carton of 60s | 64253-020-30

*in 6 mL Syringe **in 12 mL Syringe

Discard unused portion

Store at 20 to 25°C (68 to 77°F). [See USP Controlled Room Temperature.]. Protect from freezing